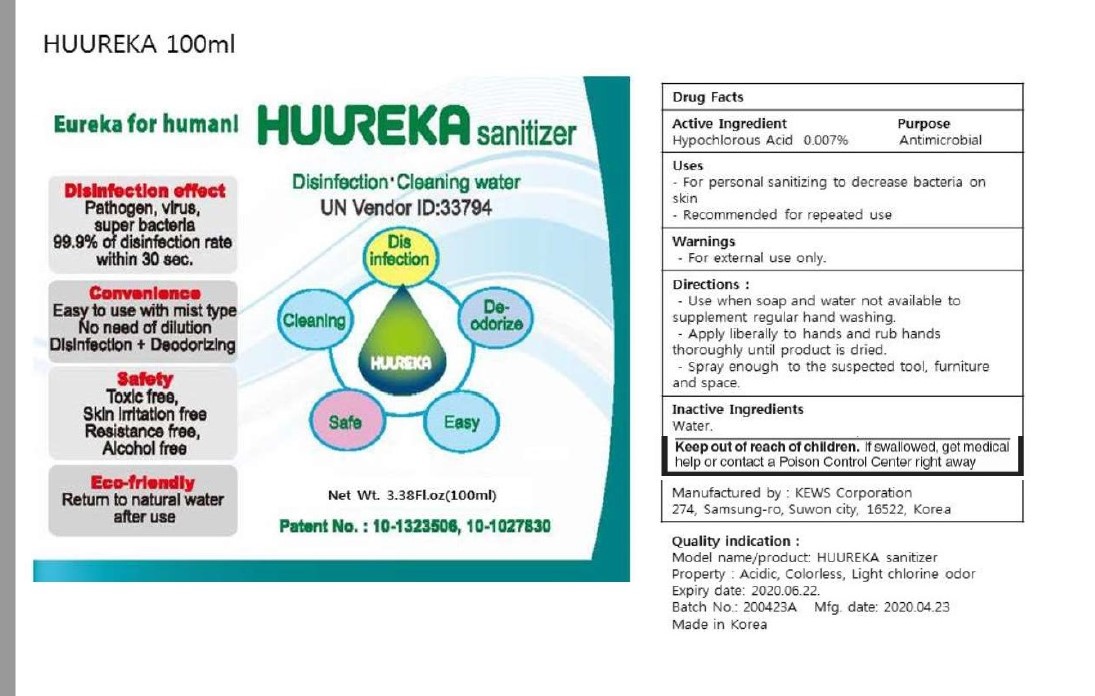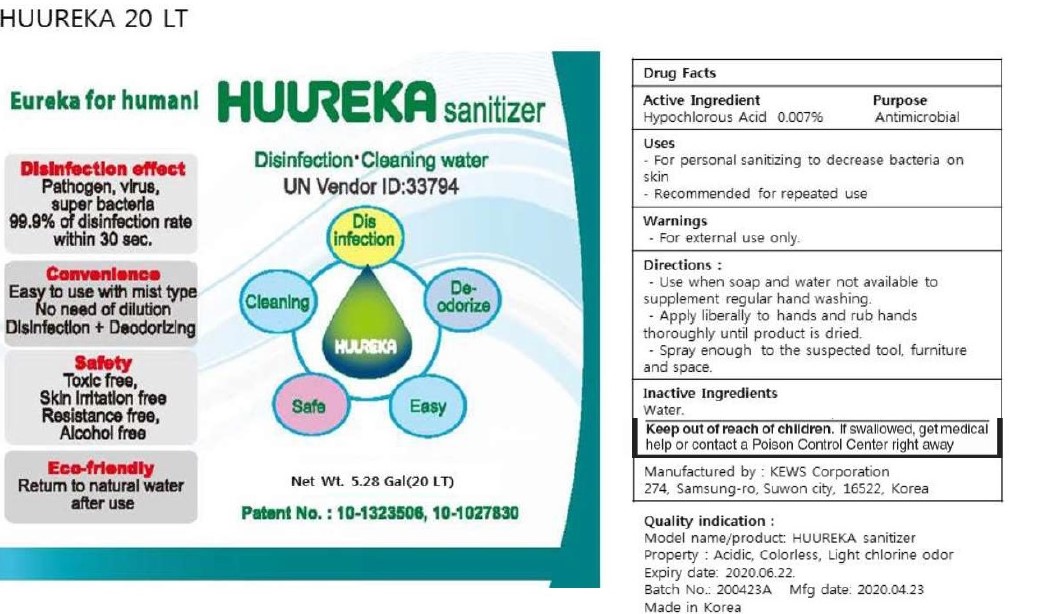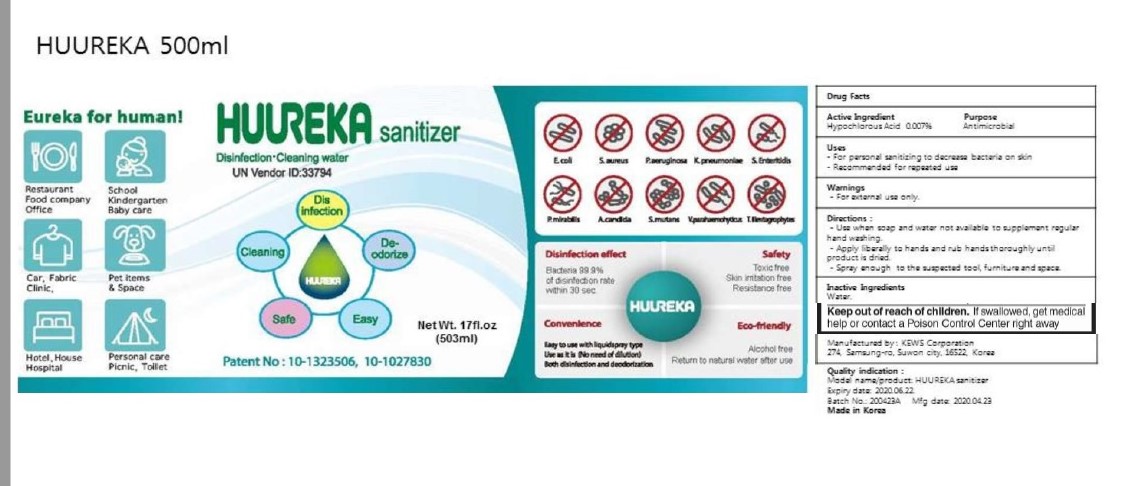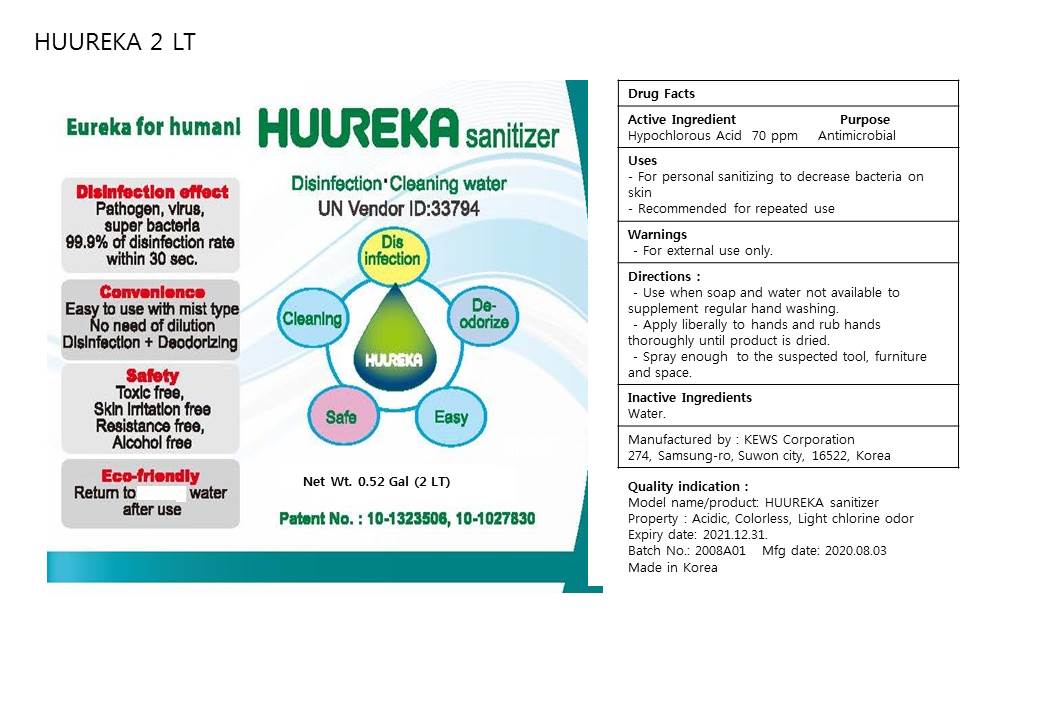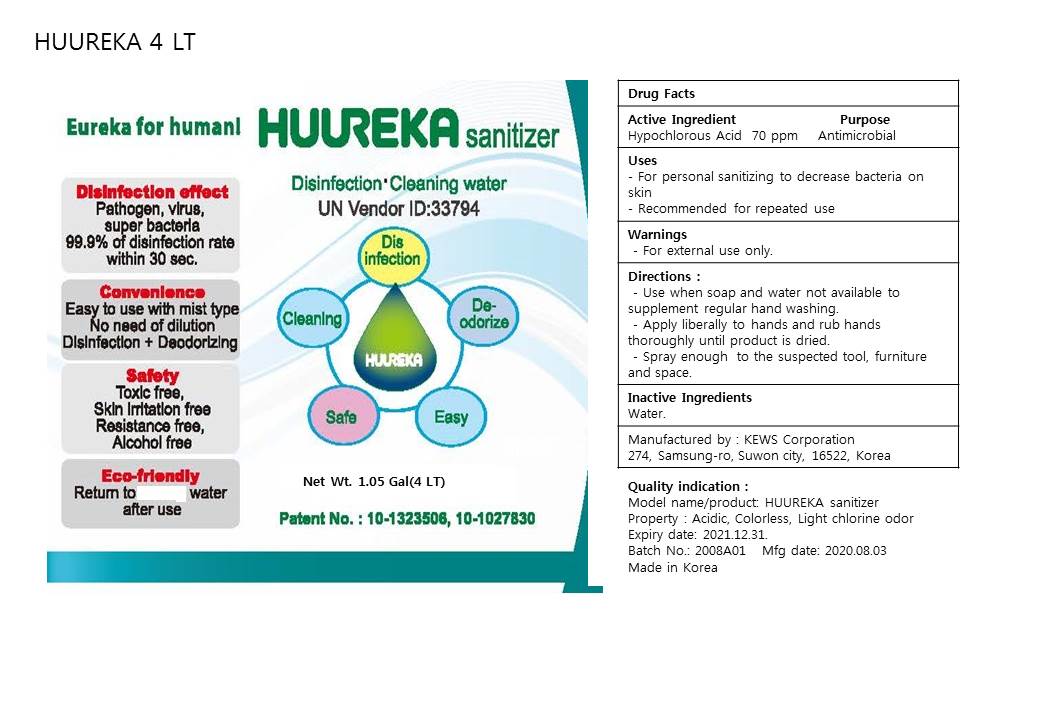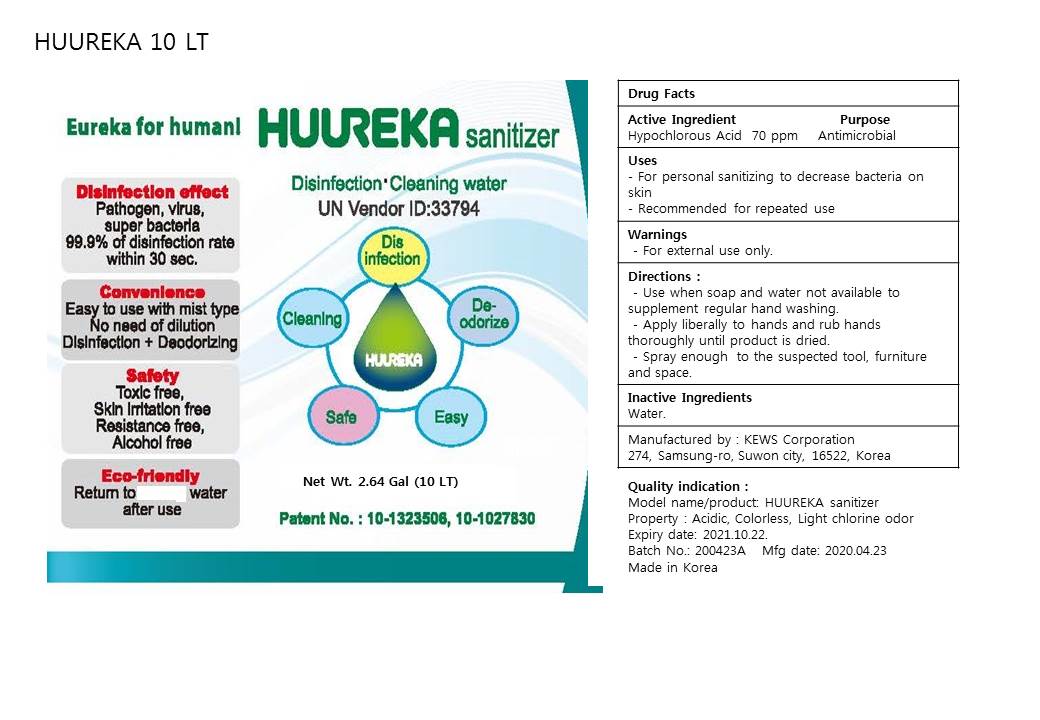 DRUG LABEL: HUUREKA SANITIZER
NDC: 75644-001 | Form: LIQUID
Manufacturer: KEWS CORPORATION
Category: otc | Type: HUMAN OTC DRUG LABEL
Date: 20220118

ACTIVE INGREDIENTS: HYPOCHLOROUS ACID 0.007 mg/1 mL
INACTIVE INGREDIENTS: WATER

HUUREKA SANITIZER

Active Ingredient

Hypochlorous Acid ------ 0.0.007%

Purpose

Antimicrobial

Directions for Use:

Use when soap and water not available to supplement regular hand washing.

Apply liberally to hands and rub hands thoroughly until product is dried.

Spray enough to the suspected tool, furniture and space.

Inactive Ingredient(s)

Water

Intended Use

For Personal sanitizing to decrease baceteria on skin

Recommended for repeated use.

Warnings:

For External Use

Purpose:

For personal sanitizing to decrease bacteria on skin.

Recommened for repeated use.

Keep out of reach of children.

If swallowed, get medical help or contact a Poison Control Center right away.

100 mL PDP

100mL NDC 75644-001-001

500 mL PDP

500 mL NDC 75644-001-002

2 LT PDP 75644-001-04

4 LT PDP, NDC: 75644-001-05

10 LT PDP, NDC 75644-001-06

20LT PDP

20 LT NDC 75644-001-003